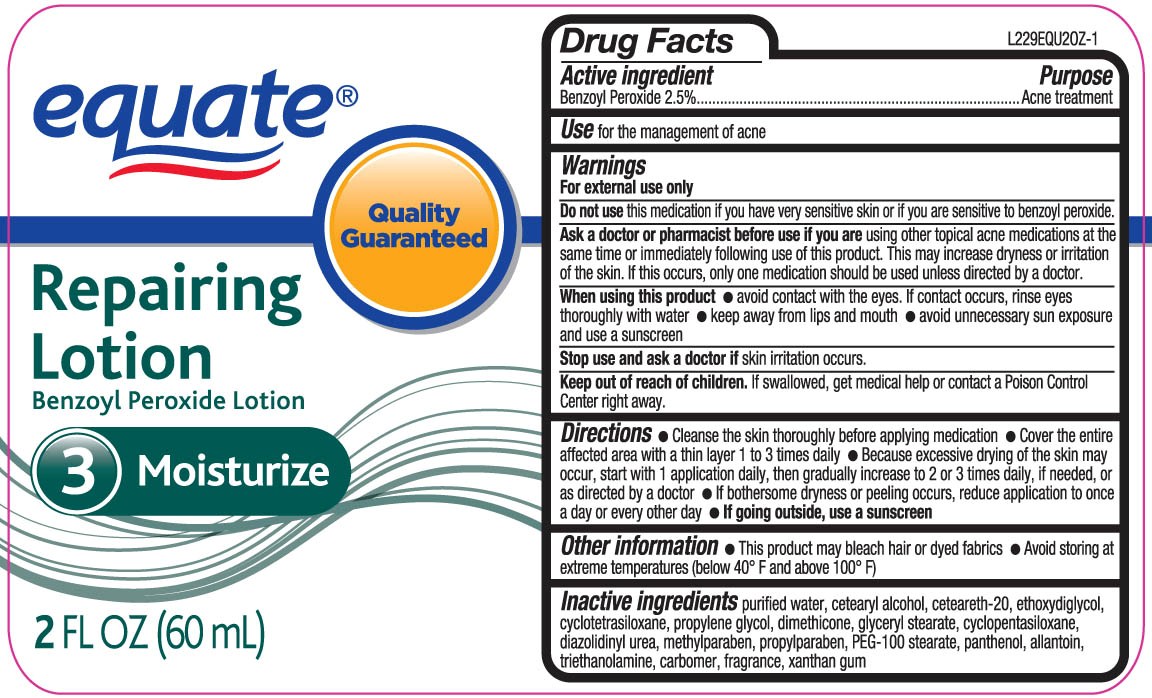 DRUG LABEL: Equate Repairing
NDC: 49035-020 | Form: LOTION
Manufacturer: Wal-Mart Stores Inc
Category: otc | Type: HUMAN OTC DRUG LABEL
Date: 20120426

ACTIVE INGREDIENTS: BENZOYL PEROXIDE 25 mg/1 mL
INACTIVE INGREDIENTS: WATER; DIETHYLENE GLYCOL MONOETHYL ETHER; GLYCERYL MONOSTEARATE; PEG-100 STEARATE; CETOSTEARYL ALCOHOL; POLYOXYL 20 CETOSTEARYL ETHER; PROPYLENE GLYCOL; DIMETHICONE; HEXAMETHYLDISILOXANE; CYCLOMETHICONE 5; DEXPANTHENOL; ALLANTOIN; XANTHAN GUM; CARBOMER HOMOPOLYMER TYPE B/C (ALLYL PENTAERYTHRITOL CROSSLINKED); TROLAMINE; DIAZOLIDINYL UREA; METHYLPARABEN; PROPYLPARABEN

drug facts

Active ingredient Purpose
Benzoyl Peroxide, 2.5%.......................................Acne Treatment

PURPOSE

Use - for the management of acne

Keep out of reach of children.If swallowed, get medical help or contact a Poison
Control Center right away.

Directions

- cleanse the skin thoroughly before applying medication.
- cover the entire affected area with a thin film 1-3 times daily
- because excessive drying of the skin may occur, start with 1 application daily and then increase to 2 or 3 times if needed or as directed by a doctor.
- if bothersome drying or peeling occurs, reduce application to once a day or every other day
- if going outside, use a sunscreen
Other Information
- this product may bleach hair or dyed fabrics
- avoid storing at extreme temperatures (below 40 degrees F and above 100 degrees F)

Warnings
For external use only.
Do not use this medication if you have very sensitive skin or if you are sensitive to benzoyl peroxide.
Ask a doctor or pharmacist before use if you are using other topical acne medications at the same time or immediately following the use of this product.
This may increase dryness or irritation of the skin. If this occurs, only one medication should be used unless directed by a doctor.
When using this product
- avoid contact with the eyes. If contact occurs, rinse eyes thoroughly with water
- Keep away from lips and mouth
- Avoid unnecessary sun exposure and use a sunscreen
Stop use and ask a doctor if skin irritation occurs.
Keep out of reach of children. If swallowed, get medical help or contact a Poison Control Center right away.

Directions

- cleanse the skin thoroughly before applying medication.
- cover the entire affected area with a thin film 1-3 times daily
- because excessive drying of the skin may occur, start with 1 application daily and then increase to 2 or 3 times if needed or as directed by a doctor.
- if bothersome drying or peeling occurs, reduce application to once a day or every other day
- if going outside, use a sunscreen
Other Information
- this product may bleach hair or dyed fabrics
- avoid storing at extreme temperatures (below 40 degrees F and above 100 degrees F)

INACTIVE INGREDIENT

Inactive Ingredients purified water, cetearyl alcohol, ceteraeth-20, ethoxydiglycol, cyclotetrasilozane, propylene glycol, dimethicone,
glyceryl stearate, cyclopentasiloxane, diazolidinyl urea, methylparaben, propylparaben, PEG-100 stearate, panthenol, allantonin, triethanolamine,
carbomer, fragrance, xanthan gum